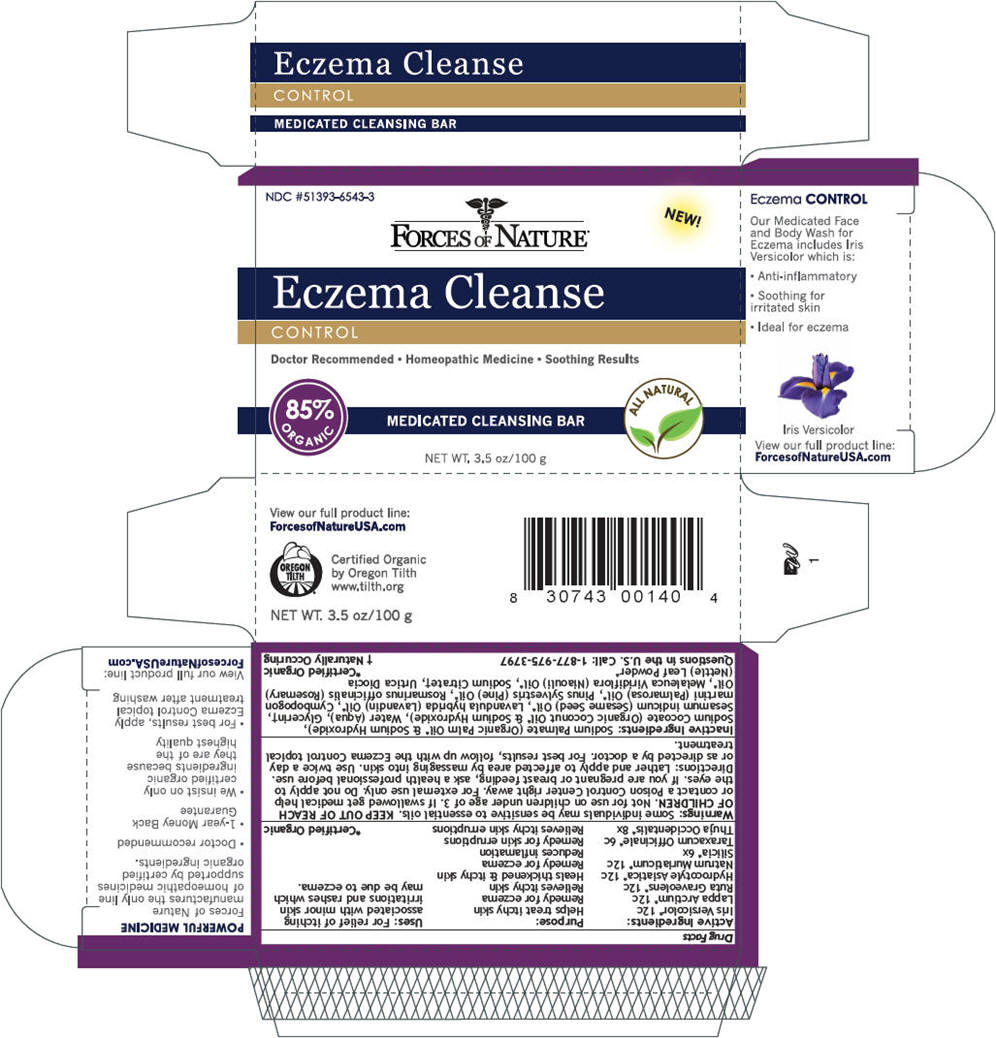 DRUG LABEL: Eczema Cleanse
NDC: 51393-6543 | Form: SOAP
Manufacturer: Forces of Nature
Category: homeopathic | Type: HUMAN OTC DRUG LABEL
Date: 20131031

ACTIVE INGREDIENTS: Iris Versicolor Root 12 [hp_C]/100 g; Arctium Lappa Root 12 [hp_C]/100 g; Ruta Graveolens Flowering Top 12 [hp_C]/100 g; Centella Asiatica 12 [hp_C]/100 g; Sodium Chloride 12 [hp_C]/100 g; Silicon Dioxide 6 [hp_X]/100 g; Taraxacum Officinale 6 [hp_C]/100 g; Thuja Occidentalis Leafy Twig 8 [hp_X]/100 g
INACTIVE INGREDIENTS: Sodium Palmate; Sodium Cocoate; Water; Glycerin; Sesame Oil; Lavandin Oil; Palmarosa Oil; White Pine Oil; Rosemary Oil; Niaouli Oil; Sodium Citrate; Urtica Dioica

Eczema Cleanse

Drug Facts

ACTIVE INGREDIENT

Active Ingredients: | Purpose:
Iris Versicolor [Certified Organic] 12c | Helps treat itchy skin
Lappa Arctium 12c | Remedy for eczema
Ruta Graveolens 12c | Relieves itchy skin
Hydrocotyle Asiatica 12c | Heals thickened & itchy skin
Natrum Muriaticum 12c | Remedy for eczema
Silicia 6x | Reduces inflamation
Taraxacum Officinale 6c | Remedy for skin erruptions
Thuja Occidentalis 8x | Relieves itchy skin erruptions

Uses

For relief of itching associated with minor skin irritations and rashes which may be due to eczema.

Warnings

Some individuals may be sensitive to essential oils.

KEEP OUT OF REACH OF CHILDREN. Not for use on children under age of 3. If swallowed get medical help or contact a Poison Control Center right away. For external use only.

WHEN USING

Do not apply to the eyes.

PREGNANCY OR BREAST FEEDING

If you are pregnant or breast feeding, ask a health professional before use.

Directions

Lather and apply to affected area by massaging into skin. Use twice a day or as directed by a doctor. For best results, follow up with the Eczema Control topical treatment.

Inactive Ingredients

Sodium Palmate (Organic Palm Oil [Certified Organic] & Sodium Hydroxide), Sodium Cocoate (Organic Coconut Oil & Sodium Hydroxide), Water (Aqua), Glycerin [Naturally Occuring] , Sesamum indicum (Sesame Seed) Oil, Lavandula hybrida (Lavandin) Oil, Cymbopogon martini (Palmarosa) Oil, Pinus Sylvestris (Pine) Oil, Rosmarinus officinalis (Rosemary) Oil, Melaleuca Viridiflora (Niaouli) Oil, Sodium Citrate, Urtica Diocia (Nettle) Leaf Powder

Questions in the U.S. Call

1-877-975-3797

PRINCIPAL DISPLAY PANEL - 100 g Box

NDC #51393-6543-3

NEW!

FORCES OF NATURE®

Eczema Cleanse

CONTROL

Doctor Recommended • Homeopathic Medicine • Soothing Results

85%
ORGANIC

MEDICATED CLEANSING BAR

ALL NATURAL

NET WT. 3.5 oz/100 g